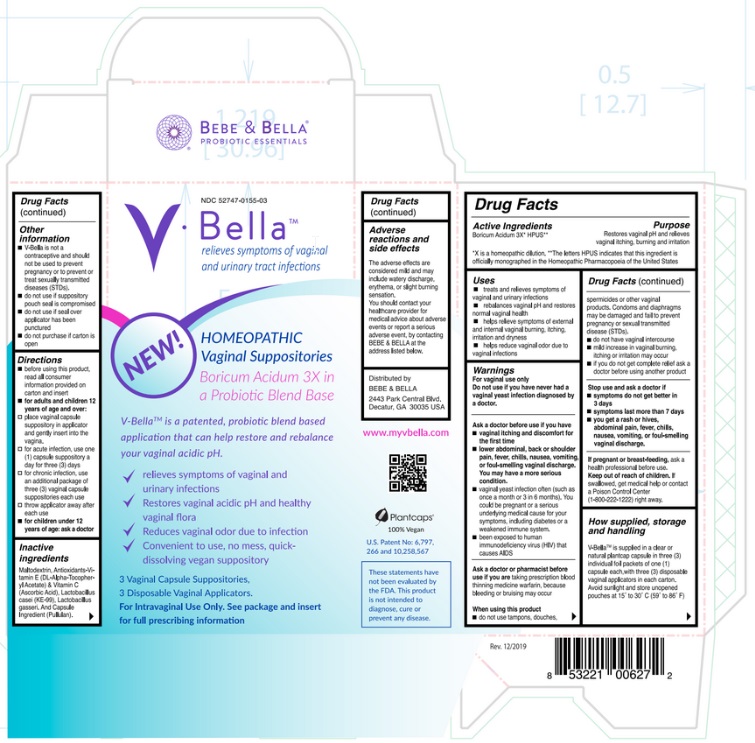 DRUG LABEL: V-Bella
NDC: 52747-155 | Form: SUPPOSITORY
Manufacturer: U.S. PHARMACEUTICAL CORPORATION
Category: homeopathic | Type: HUMAN OTC DRUG LABEL
Date: 20221117

ACTIVE INGREDIENTS: BORIC ACID 3 [hp_X]/1 1
INACTIVE INGREDIENTS: MALTODEXTRIN; .ALPHA.-TOCOPHEROL ACETATE, DL-; ASCORBIC ACID; LACTICASEIBACILLUS CASEI; LACTOBACILLUS GASSERI; PULLULAN

Active Ingredient

Boricum Acidum 3X* HPUS**

*X is a homeopathic dilution. **The letters HPUS indicates that this ingredient is officially monographed in the Homeopathic Pharmacopoeia of the United States.

Purpose

Restores vaginal pH and relieves vaginal itching, burning and irritation.

Uses

- treats and relieves symptoms of vaginal and urinary infections.
- rebalances vaginal pH and restores normal vaginal health.
- helps relieve symptoms of external and internal vaginal burning, itching, irritation and dryness.
- helps reduce vaginal odor due to vaginal infections.

Warnings

For vaginal use only

Do not use if you have never had a vaginal yeast infection diagnosed by a doctor.

Ask a doctor before use if you have

- vaginal itching and discomfort for the first time
- lower abdominal, back or shoulder pain, fever, chills, nausea, vomiting, or foul-smelling vaginal discharge. You may have a more serious condition.
- vaginal yeast infection often (such as once a month or 3 in 6 months). You could be pregnant or a serious underlying medical cause for your symptoms, including diabetes or a weakened immune system.
- been exposed to human immunodeficiency virus (HIV) that causes AIDS.

Ask a doctor or pharmacist before use if you are taking prescription blood thinning medicine warfarin, because bleeding or bruising may occur.

When using this product

- do not use tampons, douches, spermicides or other vaginal products. Condoms and diaphragms may be damaged and fail to prevent pregnancy or sexual transmitted disease (STDs).
- do not have vaginal intercourse
- mild increase in vaginal burning, itching or irritation may occur
- if you do not get complete relief ask a doctor before using another product

Stop use and ask a doctor if

- symptoms do not get better in 3 days
- symptoms last more than 7 days
- you get a rash or hives, abdominal pain, fever, chills, nausea, vomiting, or foul-smelling vaginal discharge.

If pregnant or breast-feeding, ask a health professional before use.

Keep out of reach of children. If swallowed, get medical help or contact a Poison Control Center (1- 800-222-1222) right away.

How supplied, storage and handling
V-Bella ™ is supplied in a clear natural plantcap capsule in three (3) individual foil packets of one (1) capsule each, NDC # 52747-0155-03 with three (3) disposable vaginal applicators in each carton.
Avoid sunlight and store unopened pouches at 15˚ to 30˚ C (59˚ to 86˚ F)

Other information
V-Bella ™ is not a contraceptive and should not be used to prevent pregnancy or to prevent or treat sexually transmitted diseases (STDs).

- do not use if suppository pouch seal is compromised
- do not use if seal over applicator has been punctured
- do not purchase if carton is open

Directions

- before using this product, read all consumer information provided on carton and insert,
- Adults and children 12 years of age and over:
- place vaginal capsule suppository in applicator and gently insert into the vagina.
- for acute infection, use one (1) capsule suppository a day for three (3) days
- for chronic infection, use an additional package of three (3) vaginal capsule suppositories
- throw applicator away after each use

Children under 12 years of age: ask a doctor

Other information

- Store between 15-30C (59-86F)
- Avoid freezing and excessive heat above 40C (104F)

Inactive ingredients

Maltodextrin, Antioxidants-Vitamin E (DL-Alpha-Tocopheryl Acetate) & Vitamin C (Ascorbic Acid), Lactobacillus casei (KE-99), Lactobacillus gasseri and Capsule Ingredient (Pullulan). Adverse reactions and side effects
The adverse effects are considered mild and may include watery discharge, erythema, or slight burning sensation.
You should contact your healthcare provider for medical advice about adverse events or report a serious adverse event, by contacting BeBe & Bella, LLC. at the address listed below.

Distributed by:

BeBe & Bella, LLC
2443 Park Central Blvd.
Decatur, GA 30035, USA